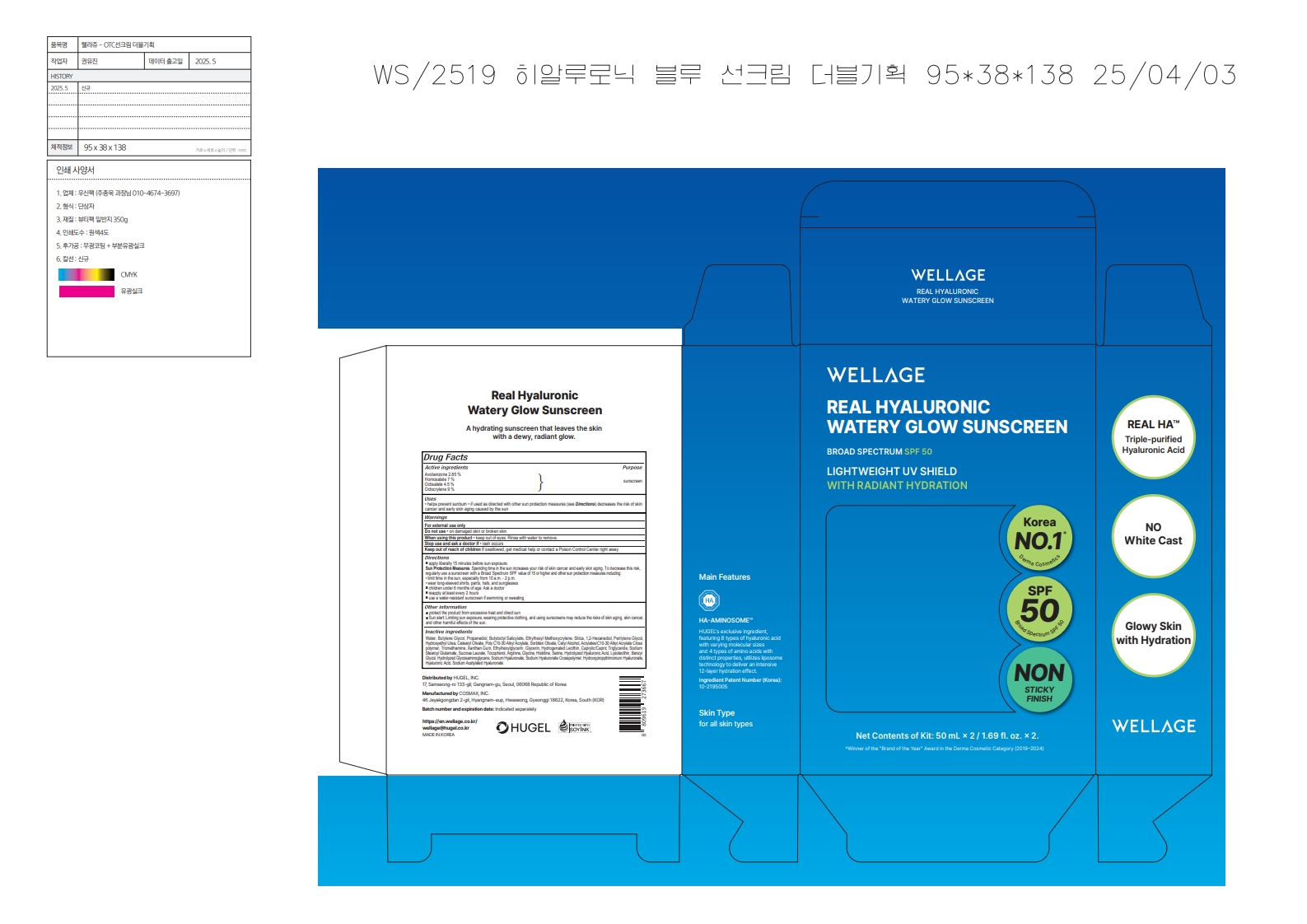 DRUG LABEL: Wellage Real Hyaluronic Watery Glow Sun Screen
NDC: 81165-001 | Form: CREAM
Manufacturer: Hugel, Inc.
Category: otc | Type: HUMAN OTC DRUG LABEL
Date: 20250616

ACTIVE INGREDIENTS: HOMOSALATE 3.5 g/50 mL; OCTISALATE 2.25 g/50 mL; AVOBENZONE 1.425 g/50 mL; OCTOCRYLENE 4.5 g/50 mL
INACTIVE INGREDIENTS: ETHYLHEXYL METHOXYCRYLENE; SILICA; PENTYLENE GLYCOL; HYDROXYETHYL UREA; SERINE; SODIUM HYALURONATE; SODIUM ACETYLATED HYALURONATE; PROPANEDIOL; CETYL ALCOHOL; TOCOPHEROL; BUTYLENE GLYCOL; BUTYLOCTYL SALICYLATE; XANTHAN GUM; ETHYLHEXYLGLYCERIN; SORBITAN OLIVATE; SUCROSE LAURATE; 1,2-HEXANEDIOL; CETEARYL OLIVATE; HYALURONIC ACID; TROMETHAMINE; GLYCERIN; CAPRYLIC/CAPRIC TRIGLYCERIDE; SODIUM STEAROYL GLUTAMATE; ARGININE; BENZYL GLYCOL; WATER; GLYCINE; HISTIDINE

Hugel, Inc. Wellage Real Hyaluronic Watery Glow Sun Screen

Active ingredients

Avobenzone 2.85 %

Homosalate 7 %

Octisalate 4.5 %

Octocrylene 9 %

Purpose

sunscreen

Uses

• helps prevent sunburn • if used as directed with other sun protection measures (see Directions) decreases the risk of skin cancer and early skin aging caused by the sun

Warnings

For external use only

Do not use

- on damaged skin or broken skin

When using this product

- keep out of eyes. Rinse with water to remove.

Stop use and ask a doctor if

- rash occurs

Keep out of reach of children

If swallowed, get medical help or contact a Poison Control Center right away.

Directions

■ apply liberally 15 minutes before sun exposure.
Sun Protection Measures. Spending time in the sun increases your risk of skin cancer and early skin aging. To decrease this risk, regularly use a sunscreen with a Broad Spectrum SPF value of 15 or higher and other sun protection measures including:
• limit time in the sun, especially from 10 a.m. - 2 p.m.
• wear long-sleeved shirts, pants, hats, and sunglasses
■ children under 6 months of age: Ask a doctor
■ reapply at least every 2 hours
■ use a water-resistant sunscreen if swimming or sweating

Other information

■ protect the product from excessive heat and direct sun
■ Sun alert: Limiting sun exposure, wearing protective clothing, and using sunscreens may reduce the risks of skin aging, skin cancer, and other harmful effects of the sun.

Inactive ingredients

Water, Butylene Glycol, Propanediol, Butyloctyl Salicylate, Ethylhexyl Methoxycrylene, Silica, 1,2-Hexanediol, Pentylene Glycol, Hydroxyethyl Urea, Cetearyl Olivate, Poly C10-30 Alkyl Acry- late, Sorbitan Olivate, Cetyl Alcohol, Acrylates/ C10-30 Alkyl Acrylate Crosspolymer, Trometha- mine, Xanthan Gum, Ethylhexylglycerin, Glycerin, Hydrogenated Lecithin, Caprylic/Capric Trigly- ceride, Sodium Stearoyl Glutamate, Sucrose Laurate, Tocopherol, Arginine, Glycine, Histidine, Serine, Hydrolyzed Hyaluronic Acid, Lysolecithin, Benzyl Glycol, Hydrolyzed Glycosaminoglycans, Sodium Hyaluronate, Sodium Hyaluronate Cross- polymer, Hydroxypropyltrimonium Hyaluronate, Hyaluronic Acid, Sodium Acetylated Hyaluronate